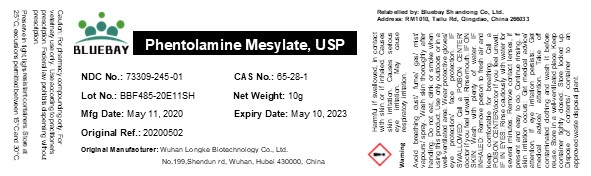 DRUG LABEL: Phentolamine Mesylate
NDC: 73309-245 | Form: POWDER
Manufacturer: BLUEBAY SHANDONG CO.,LTD
Category: other | Type: BULK INGREDIENT
Date: 20210129

ACTIVE INGREDIENTS: PHENTOLAMINE MESYLATE 1 g/1 g

Phentolamine Mesylate